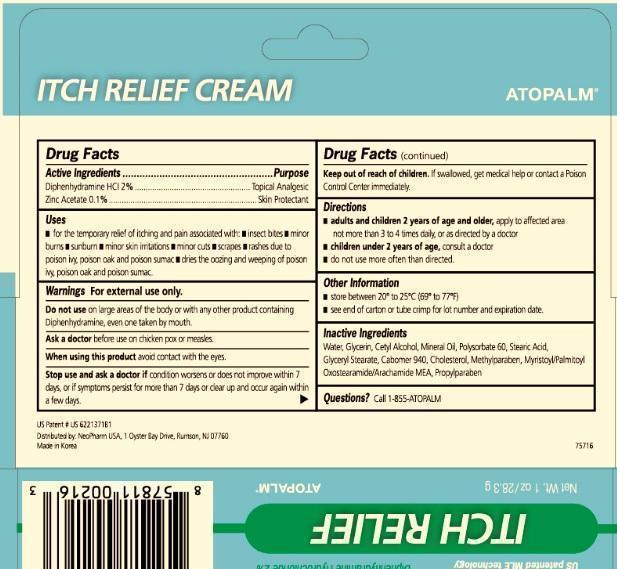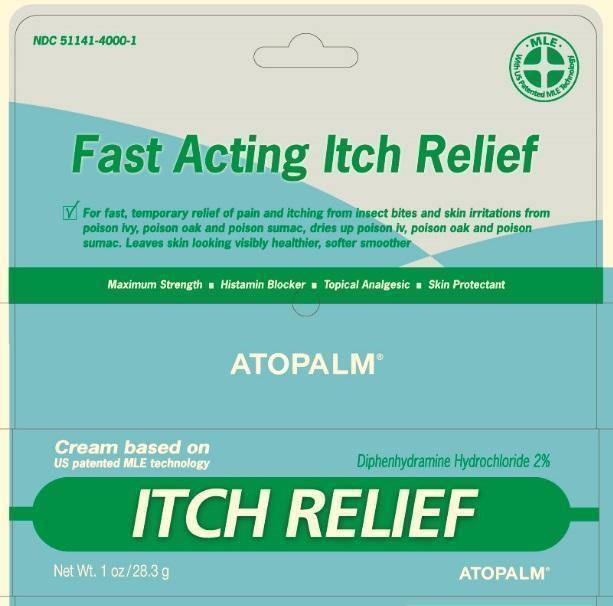 DRUG LABEL: Atopalm Itch Relief
                        
NDC: 51141-4000 | Form: CREAM
Manufacturer: Neopharm Co, Ltd
Category: otc | Type: HUMAN OTC DRUG LABEL
Date: 20150605

ACTIVE INGREDIENTS: DIPHENHYDRAMINE HYDROCHLORIDE 2 g/100 g; ZINC ACETATE 0.1 g/100 g
INACTIVE INGREDIENTS: WATER; GLYCERIN; CETYL ALCOHOL; MINERAL OIL; POLYSORBATE 60; STEARIC ACID; GLYCERYL MONOSTEARATE; CARBOMER HOMOPOLYMER TYPE C; CHOLESTEROL; METHYLPARABEN; MYRISTOYL/PALMITOYL OXOSTEARAMIDE/ARACHAMIDE MEA; PROPYLPARABEN

Atopalm Itch Relief Cream

Active Ingredient

Diphenhydramine HCl 2%

Zinc Acetate 0.1%

Purpose

Topical Analgesic

Skin protectant

Uses

For the temporary relief of itching and pain associated with
insect bites
minor burns
sunburn
minor skin irritations
minor cuts
scrapes
rashes due to poison ivy, poison oak and poison sumac
dries the oozing and weeping of poison ivy, poison oak, and poison sumac

Warnings:

For external use only.

Do not use

on large areas of the body or with any other product containing Diphenhydramine, even one taken by mouth.

Ask a doctor before use on chicken pox or measles.

When using this product

avoid contact with the eyes

Stop use and ask a doctor if

condition worsens or does not improve within 7 days, or if symptoms persist for more than 7 days or clear up and occur again within a few days.

Keep out of reach of children

If swallowed, get medical help or contact a Poison Control Center immediately.

Directions

adults and children 2 years of age and older, apply to affected area no more than 3 to 4 times daily, or as directed by a doctor.
children under 2 years of age, consult a doctor.
do not use more often than directed

Other information

store between 20C to 25C (69F to 77F)
see end of carton or tube crimp for lot number and expiration date.

Inactive Ingredients

Water, Glycerin, Cetyl Alcohol, Mineral Oil, Polysorbate 60, Stearic Acid, Glyceryl sterate, Carbomer 940, Cholesterol, Methylparaben, Myristoyl/Palmitoyl Oxostearamide/Arachamide MEA, propylparaben.

Questions?

Call 1-855-ATOPALM

PACKAGE LABEL

ATOPALM ITCH RELIEF CREAM

with US Patented MLE Technology

MAXIMUM STRENGTH THERAPY
TOPICAL ANALGESIC
HISTAMINE BLOCKER
SKIN PROTECTANT
For fast, temporary relief of pain and itching from insect bites and skin irritations from poison ivy, poison oak, and poison sumac, dries up poison ivy, poison oak, and poison sumac. Leaves skin looking visibly healthier, softer, smoother.
ATOPALM
Histamine Blocker
Topical Analgesic
Skin protectant

Net Wt. 1oz/28.3 g